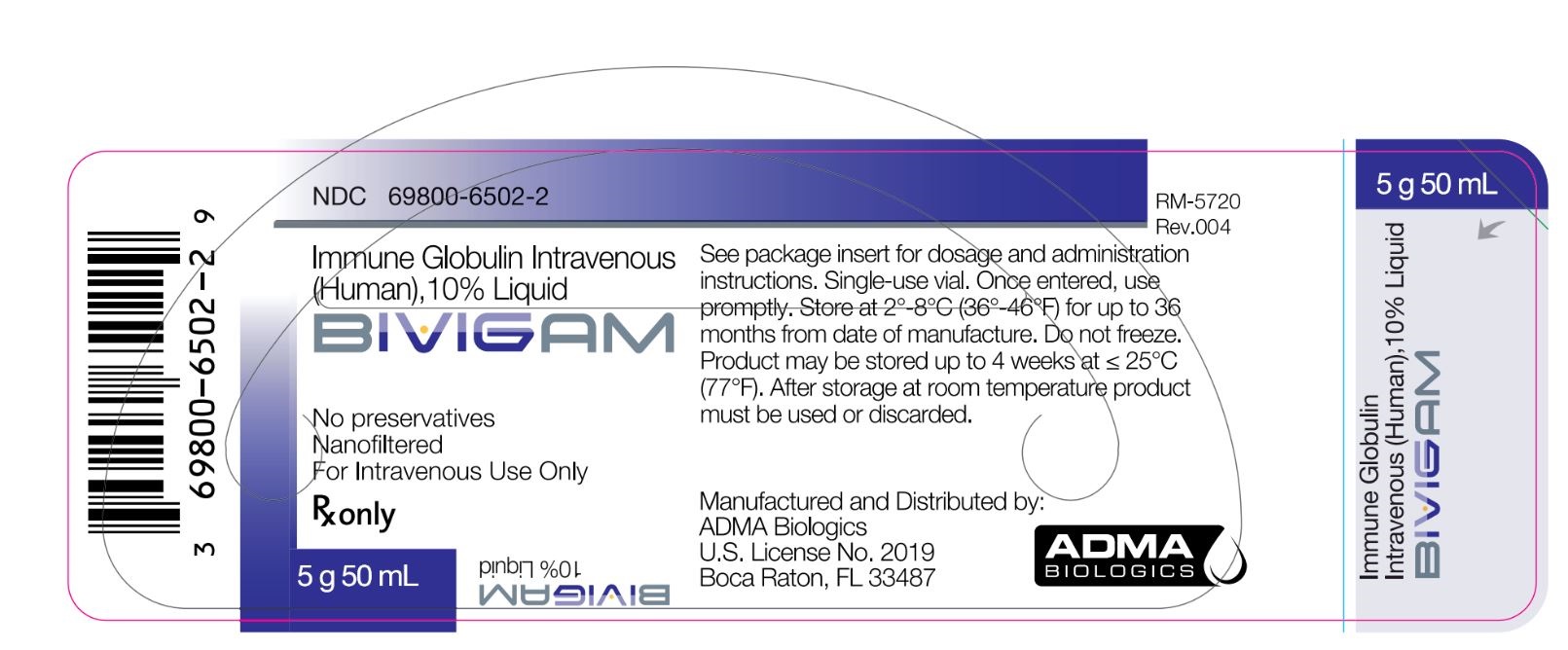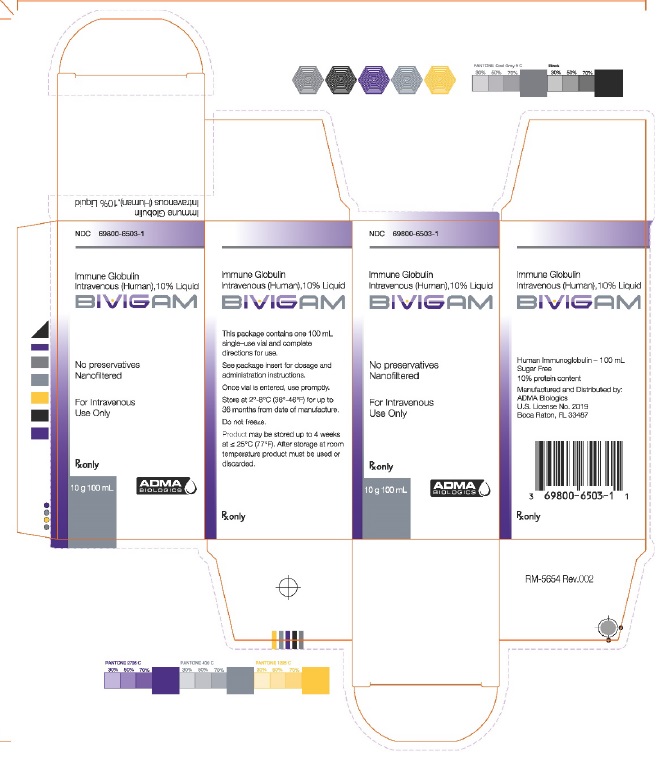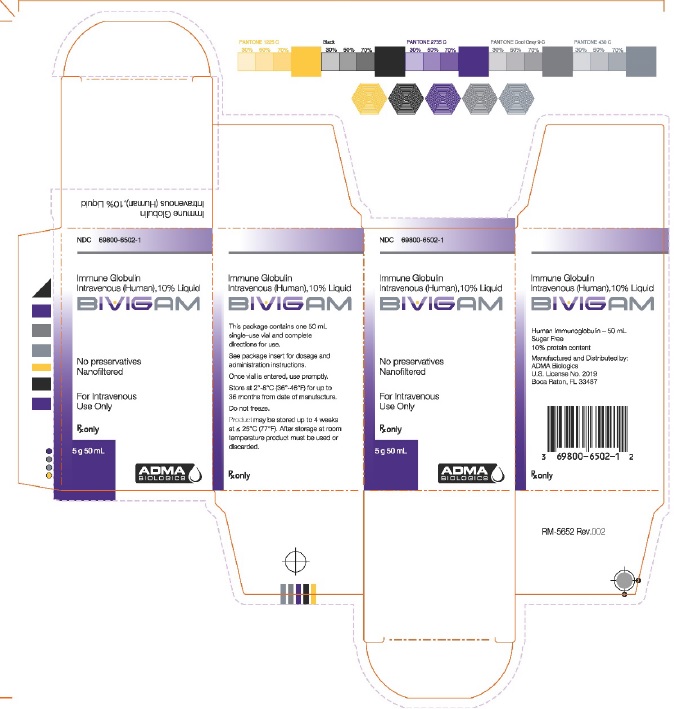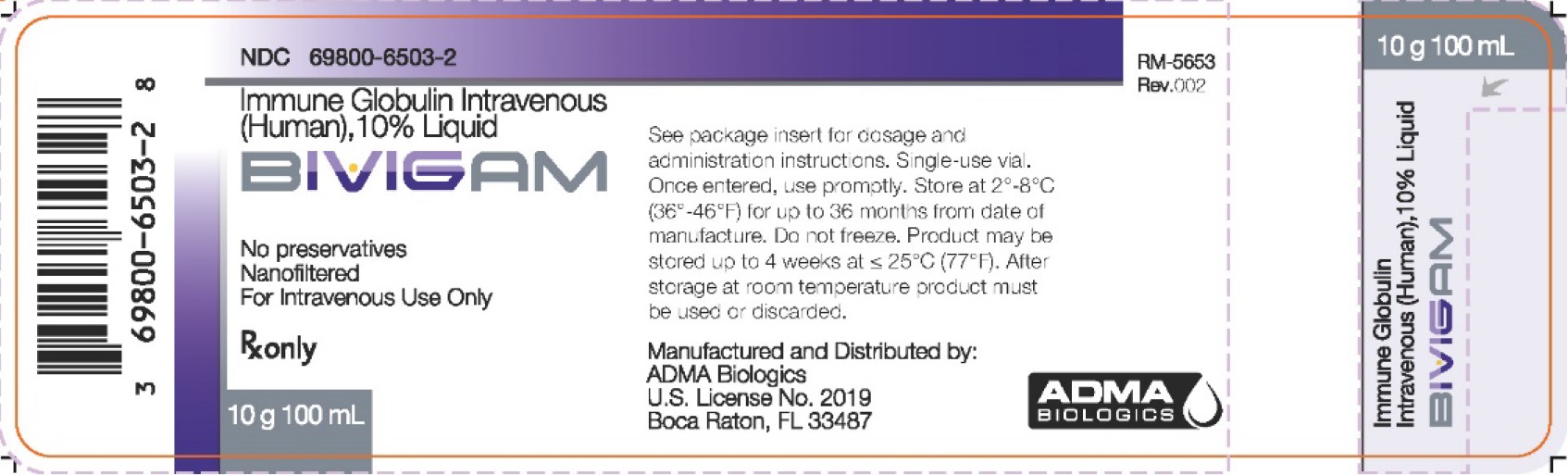 DRUG LABEL: BIVIGAM
NDC: 69800-6503 | Form: INJECTION, SOLUTION
Manufacturer: ADMA Biologics, Inc.
Category: prescription | Type: HUMAN PRESCRIPTION DRUG LABEL
Date: 20250505

ACTIVE INGREDIENTS: HUMAN IMMUNOGLOBULIN G 10 g/100 mL

HIGHLIGHTS OF PRESCRIBING INFORMATION

These highlights do not include all the information needed to use BIVIGAM® safely and effectively. See full prescribing information for BIVIGAM.
Immune Globulin Intravenous (Human), 10% Liquid
BIVIGAM
Initial U.S. Approval : 2012

WARNING: THROMBOSIS, RENAL DYSFUNCTION AND ACUTE RENAL FAILURE

See full prescribing information for complete boxed warning.

- Thrombosis may occur with immune globulin intravenous (IGIV) products, including BIVIGAM. Risk factors may include: advanced age, prolonged immobilization, hypercoagulable conditions, a history of venous or arterial thrombosis, use of estrogens, indwelling vascular catheters, hyperviscosity and cardiovascular risk factors.
- Renal dysfunction, acute renal failure, osmotic nephrosis, and death may occur with the administration of Immune Globulin Intravenous (Human) (IGIV) products in predisposed patients. [5.3]
- Renal dysfunction and acute renal failure occur more commonly in patients receiving IGIV products containing sucrose. BIVIGAM does not contain sucrose.
- For patients at risk of thrombosis, renal dysfunction or renal failure, administer BIVIGAM at the minimum dose and infusion rate practicable. Ensure adequate hydration in patients before administration. Monitor for signs and symptoms of thrombosis and assess blood viscosity in patients at risk for hyperviscosity. [2.3, 5.3]

RECENT MAJOR CHANGES

Indications and Usage, Primary Humoral Immunodeficiency (1.1) 12/2023

Dosage and Administration, Recommended Dose (2.2) 12/2023

1 INDICATIONS AND USAGE

BIVIGAM is an Immune Globulin Intravenous (Human), 10% Liquid, indicated for the treatment of adults and pediatric patients 2 years of age and older with primary humoral immunodeficiency (PI). [1]

2 DOSAGE AND ADMINISTRATION

Intravenous Use Only

Indication | Dose | Initial Infusion Rate | Maintenance Infusion Rate (if tolerated)
PI | 300-800 mg/kg every 3-4 weeks | 0.5 mg/kg/min for first 10 minutes | Increase every 20 minutes (if tolerated) by 0.8 mg/kg/min up to 6 mg/kg/min.

- Ensure that patients with pre-existing renal insufficiency are not volume depleted; discontinue BIVIGAM if renal function deteriorates. [5.3]
- For patients at risk of renal dysfunction or thrombotic events, administer BIVIGAM at the minimum infusion rate practicable. [5.1, 5.3]

3 DOSAGE FORMS AND STRENGTHS

BIVIGAM is a liquid solution containing 10% IgG (100mg/mL) for
intravenous infusion; (5g in 50mL solution, 10g in 100mL solution). [3]

4 CONTRAINDICATIONS

- History of anaphylactic or severe systemic reactions to human immunoglobulin. [4]
- IgA deficient patients with antibodies to IgA and a history of hypersensitivity. [4, 5.2]

5 WARNINGS AND PRECAUTIONS

- Thrombotic events have occurred in patients receiving IGIV therapy. Monitor patients with known risk factors for thrombotic events; consider baseline assessment of blood viscosity for those at risk of hyperviscosity. [5.1, 5.4]
- IgA deficient patients with antibodies against IgA are at greater risk of developing severe hypersensitivity and anaphylactic reactions. Have medications such as epinephrine available immediately to treat any acute severe hypersensitivity reactions. [4, 5.2]
- Monitor renal function, including blood urea nitrogen (BUN), serum creatinine, and urine output in patients at risk of developing acute renal failure. [5.3, 5.9]
- Hyperproteinemia, increased serum viscosity, and hyponatremia or pseudohyponatremia can occur in patients receiving IGIV therapy. [5.4]
- Aseptic meningitis syndrome (AMS) has been reported with IGIV treatments, especially with high doses or rapid infusion. [5.5]
- Hemolytic anemia can develop subsequent to treatment with IGIV products. Monitor patients for hemolysis and hemolytic anemia. [5.6]
- Monitor patients for pulmonary adverse reactions (Transfusion-related acute lung injury [TRALI]). If transfusion-related acute lung injury is suspected, test the product and patient for antineutrophil antibodies. [5.7]
- Because this product is made from human blood, it may carry a risk of transmitting infectious agents, e.g., viruses, and theoretically, the Creutzfeldt-Jakob disease (CJD) agent. [5.8]

6 ADVERSE REACTIONS

The most common adverse reactions to BIVIGAM (reported in ≥5% of clinical study subjects) were headache, fatigue, infusion site reaction, nausea, sinusitis, blood pressure increased, diarrhea, dizziness, and lethargy. [6]

To report SUSPECTED ADVERSE REACTIONS, contact ADMA Biologics at (800) 458-4244 or FDA at 1-800-FDA-1088 or www.fda.gov/medwatch.

7 DRUG INTERACTIONS

- Passive transfer of antibodies may transiently interfere with the immune response to live virus vaccines, such as measles, mumps, rubella, and varicella. [7]
- Passive transfer of antibodies may confound the results of serological testing. [5.10]

8 USE IN SPECIFIC POPULATIONS

- Pregnancy: Use in pregnant women has not been evaluated. Use BIVIGAM in pregnant women only if clearly needed. [8.1]
- Geriatric Use: In patients over age 65 or in any patient at risk of developing renal insufficiency, do not exceed the recommended dose, and infuse BIVIGAM at the minimum infusion rate practicable. [8.5]

FULL PRESCRIBING INFORMATION

WARNING: THROMBOSIS, RENAL DYSFUNCTION AND ACUTE RENAL FAILURE

- Thrombosis may occur with immune globulin (IGIV) products, including BIVIGAM. Risk factors may include: advanced age, prolonged immobilization, hypercoagulable conditions, history of venous or arterial thrombosis, use of estrogens, indwelling central vascular catheters, hyperviscosity and cardiovascular risk factors. Thrombosis may occur in the absence of known risk factors. (see Warnings and Precautions [5.1], Patient Counseling Information [17.2]).
- Use of Immune Globulin Intravenous (IGIV) products, particularly those containing sucrose, has been reported to be associated with renal dysfunction, acute renal failure, osmotic nephrosis, and death^1,2. Patients at risk of acute renal failure include those with any degree of pre-existing renal insufficiency, diabetes mellitus, advanced age (above 65 years of age), volume depletion, sepsis, paraproteinemia, or receiving known nephrotoxic drugs (see Warnings and Precautions [5.3]).
- Renal dysfunction and acute renal failure occur more commonly in patients receiving IGIV products containing sucrose. BIVIGAM does not contain sucrose.
- For patients at risk of thrombosis, renal dysfunction or renal failure, administer BIVIGAM at the minimum dose and infusion rate practicable. Ensure adequate hydration in patients before administration. Monitor for signs and symptoms of thrombosis and assess blood viscosity in patients at risk for hyperviscosity (see Dosage and Administration [2.2, 2.3], Warnings and Precautions [5.3]).

1 INDICATIONS AND USAGE

1.1 Primary Humoral Immunodeficiency

BIVIGAM is an Immune Globulin Intravenous (Human), 10% Liquid, indicated for the treatment of adults and pediatric patients 2 years of age and older with primary humoral immunodeficiency (PI).
This includes, but is not limited to, the humoral immune defect in common variable immunodeficiency (CVID), X-linked agammaglobulinemia, congenital agammaglobulinemia, Wiskott-Aldrich syndrome, and severe combined immunodeficiencies.

2 DOSAGE AND ADMINISTRATION

For Intravenous Use Only

2.1 Preparation and Handling

- BIVIGAM is a clear or slightly opalescent, colorless to pale yellow solution. Inspect BIVIGAM visually for particulate matter and discoloration prior to administration. Do not use if the solution is cloudy or turbid, or contains particulate matter.
- Allow refrigerated product to come to room temperature before use.
- Do not freeze or heat. Do not use any solution that has been frozen or heated.
- DO NOT SHAKE.
- Do not mix BIVIGAM with other IGIV products or other intravenous medications. If large doses of BIVIGAM are to be administered, several vials may be pooled using aseptic technique into sterile infusion bags and infused.
- Do not dilute BIVIGAM.
- BIVIGAM contains no preservatives. BIVIGAM vial is for single use only. Any vial of BIVIGAM that has been entered should be used promptly and any unused portion should be discarded immediately. Do not reuse or save for future use.
- Maintain BIVIGAM at room temperature during administration.
- Do not use after expiration date.

2.2 Recommended Dose

As there are significant differences in the half-life of IgG among patients with primary humoral immunodeficiency, the frequency and amount of immunoglobulin therapy may vary from patient to patient. The proper amount can be determined by monitoring clinical response.

The recommended dose of BIVIGAM for replacement therapy in primary humoral immunodeficiency in adults and children 2 years of age and older, is 300 to 800 mg/kg body weight administered every 3 to 4 weeks. The dosage may be adjusted over time to achieve the desired trough levels and clinical response.

BIVIGAM dose adjustments may be required in patients who fail to maintain trough total IgG concentrations of at least 500 mg/dL with a target of 600 mg/dL. Starting with the second infusion, the dose will be adjusted proportionally, targeting a trough of ≥ 600 mg/dL, based on the previous trough and the associated dose.

2.3 Administration

It has been reported that the frequency of adverse drug reactions to IGIV increases with the infusion rate. Initial infusion rates should be slow. If there are no adverse drug reactions, the infusion rate for subsequent infusions can be slowly increased to the maximum rate. For patients experiencing adverse drug reactions, it is advisable to reduce the infusion rate in subsequent infusions.

Table 1: Recommended Infusion Rates for BIVIGAM

Indication | Initial Infusion Rate (for first 10 minutes) | Maintenance Infusion Rate (if tolerated)
PI | 0.5 mg/kg/min (0.005 mL/kg/min) | Increase every 20 minutes (if tolerated) by 0.8 mg/kg/min up to 6 mg/kg/min.

Monitor patient vital signs throughout the infusion. Slow or stop the infusion if adverse reactions occur. If symptoms subside promptly, the infusion may be resumed at a lower rate that is comfortable for the patient.

Ensure that patients with pre-existing renal insufficiency are not volume depleted. For patients judged to be at risk for renal dysfunction or thrombotic events, administer BIVIGAM at the minimum infusion rate practicable, and consider discontinuation of administration if renal function deteriorates (see Boxed Warning, Warnings and Precautions [5.1, 5.3]).

3 DOSAGE FORMS AND STRENGTHS

BIVIGAM is a liquid solution containing 10% IgG (100 mg/mL) for intravenous infusion.

4 CONTRAINDICATIONS

- BIVIGAM is contraindicated in patients who have had an anaphylactic or severe systemic reaction to the administration of human immune globulin.
- BIVIGAM is contraindicated in IgA deficiency patients with antibodies to IgA and a history of hypersensitivity.

5 WARNINGS AND PRECAUTIONS

5.1 Thrombosis

Thrombosis may occur following treatment with immune globulin products (IGIV), including BIVIGAM.^4,5,6 Risk factors may include: advanced age, prolonged immobilization, hypercoagulable conditions, history of venous or arterial thrombosis, use of estrogens, indwelling central vascular catheters, hyperviscosity and cardiovascular risk factors. Thrombosis may occur in the absence of known risk factors

Consider baseline assessment of blood viscosity in patients at risk for hyperviscosity, including those with cryoglobulins, fasting chylomicronemia/markedly high triacylglycerols (triglycerides), or monoclonal gammopathies. For patients at risk of thrombosis, administer BIVIGAM at the minimum dose and infusion rate practicable. Ensure adequate hydration in patients before administration. Monitor for signs and symptoms of thrombosis and assess blood viscosity in patients at risk for hyperviscosity (see Boxed Warning, Dosage and Administration [2.3], Patient Counseling Information [17.2]).

5.2 Hypersensitivity

Severe hypersensitivity reactions may occur with IGIV products, including BIVIGAM. In case of hypersensitivity, discontinue BIVIGAM infusion immediately and institute appropriate treatment. Medications such as epinephrine should be available for immediate treatment of acute hypersensitivity reactions.

BIVIGAM contains trace amounts of IgA (≤ 200 micrograms per milliliter) (see Description [11]). Patients with known antibodies to IgA may have a greater risk of developing potentially severe hypersensitivity and anaphylactic reactions. BIVIGAM is contraindicated in IgA deficient patients with antibodies against IgA and a history of hypersensitivity reaction (see Contraindications [4]).

5.3 Acute Renal Dysfunction and Acute Renal Failure

Acute renal dysfunction/failure, osmotic nephrosis, and death^1,2 may occur upon use of human IGIV products. Ensure that patients are not volume depleted before administering BIVIGAM. Periodic monitoring of renal function and urine output is particularly important in patients judged to be at increased risk of developing acute renal failure^2. Assess renal function, including measurement of blood urea nitrogen (BUN) and serum creatinine, before the initial infusion of BIVIGAM and at appropriate intervals thereafter. If renal function deteriorates, consider discontinuing BIVIGAM (see Patient Counseling Information [17.1]). In patients who are at risk of developing renal dysfunction, because of pre-existing renal insufficiency or predisposition to acute renal failure (such as diabetes mellitus, hypovolemia, overweight, use of concomitant nephrotoxic medicinal products or age of >65 years), administer BIVIGAM at the minimum infusion rate practicable (see Dosage and Administration [2.3]).

5.4 Hyperproteinemia, Increased Serum Viscosity, and Hyponatremia

Hyperproteinemia, increased serum viscosity, and hyponatremia may occur in patients receiving IGIV therapy, including BIVIGAM. It is critical to clinically distinguish true hyponatremia from a pseudohyponatremia that is associated with or causally related to hyperproteinemia with concomitant decreased calculated serum osmolality or elevated osmolar gap, because treatment aimed at decreasing serum free water in patients with pseudohyponatremia may lead to volume depletion, a further increase in serum viscosity, and a possible predisposition to thrombotic events^3.

5.5 Aseptic Meningitis Syndrome (AMS)

AMS may occur infrequently with IGIV treatments including BIVIGAM. AMS usually begins within several hours to 2 days following IGIV treatment. Discontinuation of IGIV treatment has resulted in remission of AMS within several days without sequelae.^7,8,9

AMS is characterized by the following signs and symptoms: severe headache, nuchal rigidity, drowsiness, fever, photophobia, painful eye movements, nausea, and vomiting (see Patient Counseling Information [17.3]). Cerebrospinal fluid (CSF) studies frequently reveal pleocytosis up to several thousand cells per cubic millimeter, predominantly from the granulocytic series, and elevated protein levels up to several hundred mg/dL, but negative culture results. Conduct a thorough neurological examination on patients exhibiting such signs and symptoms, including CSF studies, to rule out other causes of meningitis.

AMS may occur more frequently in association with high doses (2 g/kg) and/or rapid infusion of IGIV.

5.6 Hemolysis

IGIV products, including BIVIGAM, may contain blood group antibodies that can act as hemolysins and induce in vivo coating of red blood cells (RBCs) with immunoglobulin, causing a positive direct antiglobulin reaction and, rarely, hemolysis.^10,11,12 Delayed hemolytic anemia can develop subsequent to IGIV therapy due to enhanced RBC sequestration,^13 and acute hemolysis, consistent with intravascular hemolysis, has been reported.

Monitor patients for clinical signs and symptoms of hemolysis (see Patient Counseling Information [17.4]). If these are present after BIVIGAM infusion, perform appropriate confirmatory laboratory testing. If transfusion is indicated for patients who develop hemolysis with clinically compromising anemia after receiving IGIV, perform adequate cross-matching to avoid exacerbating on-going hemolysis.

5.7 Transfusion-Related Acute Lung Injury (TRALI)

Noncardiogenic pulmonary edema may occur in patients following IGIV treatment^14 including BIVIGAM. TRALI is characterized by severe respiratory distress, pulmonary edema, hypoxemia, normal left ventricular function, and fever. Symptoms typically appear within 1 to 6 hours following treatment.

Monitor patients for pulmonary adverse reactions. If TRALI is suspected, perform appropriate tests for the presence of anti-neutrophil antibodies in both the product and the patient’s serum (see Patient Counseling Information [17.5]).

TRALI may be managed using oxygen therapy with adequate ventilatory support.

5.8 Transmissible Infectious Agents

Because BIVIGAM is made from human blood, it may carry a risk of transmitting infectious agents, e.g., viruses, and theoretically, the Creutzfeldt-Jakob disease (CJD) agent.

No cases of transmission of viral diseases or CJD have been associated with the use of BIVIGAM. All infections suspected by a physician possibly to have been transmitted by this product should be reported by the physician or other healthcare provider to ADMA Biologics at 1-800-458-4244. Before prescribing BIVIGAM, the physician should discuss the risks and benefits of its use with the patient (see Patient Counseling Information [17.6]).

5.9 Monitoring Laboratory Tests

- Periodic monitoring of renal function and urine output is particularly important in patients judged to be at increased risk of developing acute renal failure. Assess renal function, including measurement of blood urea nitrogen (BUN) and serum creatinine, before the initial infusion of BIVIGAM and at appropriate intervals thereafter.
- Because of the potentially increased risk of thrombosis with IGIV treatment, consider baseline assessment of blood viscosity in patients at risk for hyperviscosity, including those with cryoglobulins, fasting chylomicronemia/markedly high triacylglycerols (triglycerides), or monoclonal gammopathies.
- If signs and/or symptoms of hemolysis are present after an infusion of BIVIGAM, perform appropriate laboratory testing for confirmation.
- If TRALI is suspected, perform appropriate tests for the presence of anti-neutrophil antibodies in both the product and patient’s serum.

5.10 Interference with Laboratory Tests

After infusion of immunoglobulin, the transitory rise of the various passively transferred antibodies in the patient’s blood may yield positive serological testing results, with the potential for misleading interpretation. Passive transmission of antibodies to erythrocyte antigens (e.g., A, B, and D) may cause a positive direct or indirect antiglobulin (Coombs’) test.

6 ADVERSE REACTIONS

Serious adverse reactions observed in clinical trial subjects receiving BIVIGAM were vomiting and dehydration in one subject.

The most common adverse reactions to BIVIGAM (reported in ≥5% of clinical study subjects) were headache, fatigue, infusion site reaction, nausea, sinusitis, blood pressure increased, diarrhea, dizziness, and lethargy.

6.1 Clinical Trials Experience

Because clinical trials are conducted under widely varying conditions, adverse reaction rates observed in clinical trials cannot be directly compared to rates in the clinical trials of another product and may not reflect the rates observed in clinical practice.

In a multicenter, open-label, non-randomized clinical trial, 63 subjects with PI, on regular IGIV replacement therapy, received doses of BIVIGAM ranging from 254 to 1029 mg/kg (median dose 462.8 mg/kg) every 3 weeks or 4 weeks for up to 12 months (mean 317.3 days; range 66 – 386 days) (see Clinical Studies [14]). The use of pre-medication was discouraged; however, if subjects required pre-medication (antipyretic, antihistamine, or antiemetic agent) for recurrent reactions to immune globulins, they were allowed to continue those medications for this trial. Of the 746 infusions administered, 41 (65%) subjects received premedication prior to 415 (56%) infusions.

Fifty-nine subjects (94%) had an adverse reaction at some time during the study. The proportion of subjects who had at least one adverse reaction was the same for both the 3- and 4-week cycles. The most common adverse reactions observed in this clinical trial were headache (32 subjects, 51%), sinusitis (24 subjects, 38%), fatigue (18 subjects, 29%), upper respiratory tract infection (16 subjects, 25%), diarrhea (13 subjects, 21%), cough (14 subjects, 22%), bronchitis (12 subjects, 19%), pyrexia (12 subjects, 19%), and nausea (9 subjects, 14%).

Adverse reactions (ARs) are those occurring during or within 72 hours after the end of an infusion. In this study, the upper bound of the 1-sided 95% confidence interval for the proportion of BIVIGAM infusions with one or more temporally associated adverse reactions was 31%. The total number of adverse reactions was 431 (a rate of 0.58 ARs per infusion).

Table 2: Adverse Reactions (ARs) (within 72 hours after the end of a BIVIGAM infusion) in ≥5% of Subjects

ARs | No. Subjects Reporting ARs; (% of Subjects); [n=63] | No. Infusions With ARs; (% of Infusions); [n=746]
Headache | 27 (43%) | 115 (15.4%)
Fatigue | 15 (24%) | 59 (7.9%)
Infusion Site Reaction | 5 (8%) | 5 (0.7%)
Nausea | 5 (8%) | 8 (1.1%)
Sinusitis | 5 (8%) | 5 (0.7%)
Blood Pressure Increased | 4 (6%) | 5 (0.7%)
Diarrhea | 4 (6%) | 4 (0.5%)
Dizziness | 4 (6%) | 4 (0.5%)
Lethargy | 4 (6%) | 4 (0.5%)
Back Pain | 3 (5%) | 3 (0.4%)
Blood Pressure Diastolic Decreased | 3 (5%) | 5 (0.7%)
Fibromyalgiaa | 3 (5%) | 17 (2.3%)
Migraine | 3 (5%) | 8 (1.1%)
Myalgia | 3 (5%) | 4 (0.5%)
Pharyngolaryngeal Pain | 3 (5%) | 3 (0.4%)

a Symptoms occurring under pre-existing fibromyalgia

Seven subjects (11.1%) experienced 11 serious ARs. Two of these were related serious ARs (vomiting and dehydration) that occurred in one subject.

One subject withdrew from the study due to ARs related to BIVIGAM (lethargy, headache, tachycardia and pruritus).

All 63 subjects enrolled in this study had a negative direct antiglobulin (Coombs’) test at baseline. During the study, no subjects showed clinical evidence of hemolytic anemia.

No cases of transmission of viral diseases or CJD have been associated with the use of BIVIGAM. During the clinical trial no subjects tested positive for infection due to human immunodeficiency virus (HIV), hepatitis B virus (HBV), or hepatitis C virus (HCV). There was a single positive finding for parvovirus (B19 virus) during the study. This subject came in contact with acute B19 virus from working at a school, greeting children, where a child was reported to have symptomatic Fifth's disease. There was no cluster (no other cases in other subjects) of B19 virus transmission with the IGIV batch concerned.

Pediatric Only Study

In a prospective, open-label, single-arm, multi-center study, 16 children and adolescents with PI received doses of BIVIGAM ranging from 300 to 800 mg/kg every 3-weeks (±7 days) days (actual doses ranged from 350 mg/kg to 1077 mg/kg) or 4-weeks (±7 days) (actual doses ranged from 312 mg/kg to 693 mg/kg), for up to 5 months.

In this study, four subjects (25.0%) experienced a total of 9 adverse reactions. Adverse reactions (ARs) are those occurring during or within 72 hours after the end of an infusion. All ARs were of mild (3 events) or moderate severity (6 events). No infusion site reactions occurred during the study. No deaths and no treatment-related SAEs occurred during the study. Seven of the 96 (7.3%) BIVIGAM infusions administered were temporally associated with an adverse reaction. Two infusions were associated with more than one AR.

Table 3: Adverse Reactions (ARs) within 72 hours after the end of a BIVIGAM Infusion

Adverse Reaction (AR) | Number of Subjects Reporting AR (n=16) | % of Subjects Reporting AR (n=16) | Number of Infusions with AR (n=96) | % of Infusions with AR (n=96)
Fatigue | 1 | 6 | 2 | 2
Headache | 3 | 19 | 5 | 5
Nausea | 1 | 6 | 1 | 1
Rash | 1 | 6 | 1 | 1

6.2 Postmarketing Experience

Because postmarketing reporting of adverse reactions is voluntary and from a population of uncertain size, it is not always possible to reliably estimate the frequency of these reactions or establish a causal relationship to product exposure. The following adverse reactions have been identified and reported during the post-approval use of IGIV products:

- Respiratory: Apnea, Acute Respiratory Distress Syndrome (ARDS), Transfusion Associated Lung Injury (TRALI), cyanosis, hypoxemia, pulmonary edema, dyspnea, bronchospasm.
- Cardiovascular: Cardiac arrest, thromboembolism, vascular collapse, hypotension.
- Neurological: Coma, loss of consciousness, seizures, tremor.
- Integumentary: Stevens-Johnson syndrome, epidermolysis, erythema multiforme, bullous dermatitis.
- Hematologic: Pancytopenia, leukopenia, hemolysis, positive direct antiglobulin (Coombs’) test.
- General/Body as a Whole: Pyrexia, rigors.
- Musculoskeletal: Back pain.
- Gastrointestinal: Hepatic dysfunction, abdominal pain.

7 DRUG INTERACTIONS

7.1 Live Virus Vaccines

Immunoglobulin administration may transiently impair the efficacy of live attenuated virus vaccines such as measles, mumps, rubella, and varicella because the continued presence of high levels of passively acquired antibody may interfere with an active antibody response.^15,16 The immunizing physician should be informed of recent therapy with BIVIGAM so that appropriate measures may be taken (see Patient Counseling Information [17.7]).

8 USE IN SPECIFIC POPULATIONS

8.1 Pregnancy

No human data are available to indicate the presence or absence of drug-associated risk. Animal reproductive studies have not been conducted with BIVIGAM. It is not known whether BIVIGAM can cause fetal harm when administered to a pregnant woman or can affect reproduction capacity. Immune globulins cross the placenta from maternal circulation increasingly after 30 weeks of gestation. BIVIGAM should be given to pregnant women only if clearly needed. In the U.S. general population, the estimated background risk of major birth defects and miscarriage in clinically recognized pregnancies is 2-4% and 15-20%, respectively.

8.2 Lactation

No human data are available to indicate the presence or absence of drug-associated risk. The developmental and health benefits of breastfeeding should be considered along with the mother’s clinical need for BIVIGAM and any potential adverse effects on the breastfed infant from BIVIGAM or from the underlying maternal condition.

8.4 Pediatric Use

BIVIGAM was evaluated in 25 pediatric patients (3 children ages 2 to <6, 9 children ages 6 to <12, and 13 adolescents ages 12 to 16 years) with PI. The safety and effectiveness of BIVIGAM for the treatment of PI has been established in pediatric patients 2 years of age and older, based on data from 2 prospective, open-label, single-arm, multi-center studies, supported by evidence from a population PK analysis of adult and pediatric PK data (see Adverse Reactions [6.1], Clinical Pharmacology [12.3], and Clinical Studies [14.1]). PK, safety and efficacy were similar to those in adults. No specific dose requirements were necessary to achieve the targeted serum IgG levels in the pediatric subjects.

The safety and effectiveness of BIVIGAM has not been established in pediatric patients with PI who are under the age of 2 (see Clinical Studies [14]).

8.5 Geriatric Use

BIVIGAM should be used with caution in patients age 65 and over who are judged to be at increased risk of developing renal insufficiency or thrombotic events (see Boxed Warning, Warnings and Precautions [5.1, 5.3]). Do not exceed recommended doses and administer BIVIGAM at the minimum infusion rate practicable.

BIVIGAM was evaluated in 9 patients age 65 and older with PI. This number of geriatric patients is not sufficient to determine whether they respond differently from younger patients (see Clinical Studies [14]).

11 DESCRIPTION

BIVIGAM is a purified, sterile, ready-to-use preparation of concentrated human immunoglobulin G (IgG) antibodies. The distribution of IgG subclasses is similar to that of normal plasma.^19,20 The active ingredient is human immunoglobulin purified from source human plasma and processed using a modified classical Cohn Method 6 / Oncley Method 9 fractionation process as well as anion and cation exchange steps for added purification. BIVIGAM contains 100 ± 10 mg/mL protein, of which not less than 96% is human immunoglobulin obtained from source human plasma. It is formulated in water for injection containing 0.100-0.140 M sodium chloride, 0.20-0.29 M glycine, 0.15–0.25% polysorbate 80, and pH 4.0–4.6. BIVIGAM contains ≤ 200 µg/mL of IgA.

Each plasma donation used for the manufacture of BIVIGAM is collected from FDA licensed facilities and undergoes rigorous testing. Plasma donations must test negative for hepatitis B virus (HBV) surface antigen (HBsAg), antibodies to human immunodeficiency virus (HIV) strains 1 and 2 (anti-HIV-1/2), and antibodies to the hepatitis C virus (anti-HCV) as determined by enzyme immuno assay (EIA). In addition, each plasma unit must test negative and/or non-reactive for HIV RNA, HCV RNA, HBV DNA, Hepatitis A Virus (HAV) RNA, and Parvovirus B19 (B19 virus) DNA as determined by Nucleic Acid Amplification Testing (NAT) of plasma minipools. NAT is also performed on a sample of the manufacturing pool and must be negative and/or non-reactive for HIV RNA, HCV RNA, HBV DNA, and Hepatitis A Virus (HAV) RNA, and the limit for B19 virus DNA in a manufacturing pool is set not to exceed 10^4 IU/mL.

The manufacturing process of BIVIGAM employs six steps to remove/inactivate adventitious viruses to minimize the risk of virus transmission. The steps are "Precipitation and removal of fraction III" during cold ethanol fractionation, “Q-membrane filtration”, "Solvent/detergent treatment" (TnBP/ Triton X-100), “Anion exchange chromatography” and “virus filtration”. In compliance with current guidelines, the steps have been separately validated in a series of in vitro experiments for their capacity to inactivate or remove both enveloped and non-enveloped viruses.

Precipitation and removal of fraction III and Q-membrane filtration removes non-enveloped viruses, solvent/detergent treatment represents a virus inactivation step for enveloped viruses, Anion exchange chromatography binds enveloped and non-enveloped viruses, and virus filtration removes both enveloped and non-enveloped viruses by size exclusion. In addition to the steps above, low pH during several steps of the production process contributes to virus inactivation. The results of virus validation studies for the BIVIGAM process are shown in Table 4, expressed as log10 reduction factors.

Table 4: Virus Removal/Inactivation (log10)

Step/Virus | HIV | BVDV | SinV | WNV | PRV | MEV | EMC | BPV | PPV | SV40
Virus Type | Enveloped | Enveloped | Enveloped | Enveloped | Enveloped | Non-enveloped | Non-enveloped | Non-enveloped | Non-enveloped | Non-enveloped
Virus Family | Retro | Flavi | Flavi | Flavi | Herpes | Picorna | Picorna | Parvo | Parvo | Polyoma
Precipitation and Removal of Fraction III and Depth; Filtration | - | - | - | - | - | 5.29 | ≥5.70 | - | ≥5.78 | 2.00*
Q-Membrane Filtration^1 | - | - | - | - | - | - | - | - | 2.02 | -
Solvent - DetergentTNBP/Triton X- 100; Treatment | ≥3.92 | ≥5.32 | >7.11 | >4.96 | ≥4.88 | - | - | - | - | -
Anion Exchange Chromatography | 1.04 | - | - | - | - | - | - | - | 1.09 | -
Virus Nanofiltration | ≥4.72 | ≥4.67 | - | - | ≥4.15 | - | ≥6.24 | 6.18 | 4.66 | >5.02
Low pH Treatment^2 | 2.43 | - | - | - | 3.20^2 | - | - | - | - | -
Total Clearance | ≥9.68 | ≥9.99 | >7.11 | >4.96 | ≥12.23 | 5.29 | ≥5.70^3 | 6.18 | 11.49 | >7.02

* without depth filtration

HIV, human immunodeficiency virus; BVDV, Bovine viral diarrhea virus, model virus for HCV; SinV, Sindbis virus, model virus for HCV; WNV, West Nile virus; PRV, Pseudorabies virus, model virus for herpes viruses and Hepatitis B virus; MEV, Murine encephalomyelitis virus, model virus for hepatitis A virus; BPV, Bovine parvovirus, model virus for human B19 virus; PPV, Porcine parvovirus, model virus for human B19 virus; SV40, Simian virus 40, model virus for highly resistant non- enveloped viruses. EMC, Encephalomyocarditis virus, model virus for hepatitis A virus.

1 Q-membrane filtration step is associated with the affinity stream part of the production process.

2 Low pH treatment included in total clearance calculation based on separate mode of inactivation than VRF.

3 EMC total clearance was calculated with the most conservative approach of using the lowest reduction value (>5.70) between the Fraction III precipitation/ filtration and nanofiltration steps.

12 CLINICAL PHARMACOLOGY

12.1 Mechanism of Action

BIVIGAM is a replacement therapy in patients with primary humoral immunodeficiency (PI) (e.g. agammaglobulinaemia, hypogammaglobulinaemia, CVID, SCID).

The broad spectrum of neutralizing IgG antibodies against bacterial and viral pathogens and their toxins helps to avoid recurrent serious opportunistic infections. IgG antibodies are opsonins that increase phagocytosis and elimination of pathogens from the circulation. The mechanism of action has not been fully elucidated in PI.

12.2 Pharmacodynamics

BIVIGAM contains mainly immunoglobulin G (IgG) with a broad spectrum of antibodies against various infectious agents, reflecting the IgG activity found in the donor population. BIVIGAM, which is prepared from pooled plasma from not less than 1,000 donors, has an IgG subclass distribution similar to that of native human plasma. Adequate doses of IGIV can restore an abnormally low IgG level to the normal range. Standard pharmacodynamics studies were not performed.

12.3 Pharmacokinetics

In the clinical study assessing the efficacy and safety of BIVIGAM in 63 subjects with PI (see Clinical Studies [14.1]), serum concentrations of total IgG and IgG subclasses were measured in 21 subjects (ages 18 to 75) following the 4th infusion for the 5 subjects on the 3-week dosing interval and following the 5th infusion for the 16 subjects on the 4-week dosing interval. The dose of BIVIGAM used in these subjects ranged from 300 mg/kg to 800 mg/kg. After the infusion, blood samples were taken until Day 21 and Day 28 for the 3-week and 4-week dosing intervals, respectively. Table 5 summarizes the Total IgG Pharmacokinetic Parameters of BIVIGAM, based on serum concentrations of total IgG.

Table 5: Total IgG Pharmacokinetic Parameter Estimates (PK Population) in Adults

Statistic | 3-week cycle; Mean (CV%); [n=5] | 4-week cycle; Mean (CV%); [n=16] | Total; Mean (CV%); [n=21]
Cmax (mg/dL) | 2184 (13.4) | 2122 (20.0) | 2137 (18.3)
Cmin (mg/dL) | 996 (17.6) | 1106 (35.8) | 1080 (32.9)
Tmax (h)a | 4.05 (NA) | 3.47 (NA) | 3.50 (NA)
AUCtau (day*mg/dL) | 27841 (17.7) | 35509 (18.2) | 33592 (20.5)
t½ (d) | 19.6 (21.1) | 33.5 (32.0) | 30.0 (37.5)
CL (dL/d/kg) | 0.02 (11.3) | 0.01 (32.8) | 0.02 (31.0)
Vss (dL/kg) | 0.584 (22.6) | 0.640 (22.1) | 0.626 (22.0)

AUCtau = steady-state area under the plasma concentration versus time curve with tau = dosing interval; CL = total body clearance; Cmax = maximum concentration; Cmin= minimum concentration; CV = coefficient of variation; n = number of subjects; NA = not applicable; SD = standard deviation; Tmax = time of maximum concentration; t½ = terminal half-life; Vss = Volume of distribution steady-state;a Median and Range.

The median terminal half-life of BIVIGAM was 30 days for the 21 subjects. Mean trough IgG subclass levels were consistent with physiological values.

In a pediatric-only clinical study in 16 children and adolescents ≥2 to ≤16 years of age with PI, 10 subjects in the PK population contributed sufficient samples for the non-compartmental analysis of serum concentrations of total IgG and IgG subclasses after the 5th infusion (4-week regimen) or 7th infusion (3-week regimen). A population pharmacokinetic analysis was conducted using data pooled from the pediatric only clinical study together with the prior study conducted in adult and pediatric subjects with PI. Based on the pooled population pharmacokinetic analysis in 79 subjects using all evaluable total IgG PK concentrations, the clearance of BIVIGAM was similar across age groups (Table 6). After correcting for body weight no other patient-specific factors were found to affect BIVIGAM pharmacokinetics. Trough concentrations were maintained throughout the study and mean trough concentrations were well above the target trough concentration of 500 mg/dL for both treatment cycles in pediatric (≥ 2 years old) as well as adult subjects at all time points.

Table 6 Summary of Total IgG Clearance By Age Group

Age group | Number of Subjects | Mean IgG Clearance (dL/day/kg) | CV(%)
2 to <6 years | 3 | 0.01 | 6.9
6 to <12 years | 9 | 0.01 | 15.9
12 to ≤16 years | 13 | 0.01 | 21.3
>16 years | 54 | 0.01 | 24.8

CV=coefficient of variation.

13 NONCLINICAL TOXICOLOGY

13.1 Carcinogenesis, Mutagenesis, Impairment of Fertility

No animal studies were conducted to evaluate the carcinogenic or mutagenic effects of BIVIGAM or its effects on fertility.

13.2 Animal Toxicology and/or Pharmacology

No animal studies were conducted to evaluate possible toxicity of BIVIGAM in animals.

BIVIGAM contains Polysorbate 80 at a concentration of up to 2.5 mg/mL. Intravenous administrations of Polysorbate 80 in multiple species have been linked with a decrease in blood pressure. In rats, single doses of Polysorbate 80 that were up to 25 times higher than the amount from 800 mg/kg BIVIGAM resulted in an increase of liver enzymes and total bilirubin.

14 CLINICAL STUDIES

14. 1 Treatment of Primary Humoral Immunodeficiency

A prospective, open-label, single-arm, multicenter trial assessed the efficacy, safety, and pharmacokinetics of BIVIGAM in adult and pediatric subjects with PI. Study subjects were receiving regular IGIV replacement therapy, with a stable dose between 300 and 800 mg/kg for at least 3 months prior to participation. Subjects received a BIVIGAM infusion administered every 3 or 4 weeks (both the dose and schedule depending on their prior therapy) for approximately 1 year.

A total of 63 subjects were enrolled in the trial, 31 men and 32 women with a mean age of 41 years. Forty-four subjects were adults (70%) between 18 and 64 years of age. There were 9 pediatric subjects (see Pediatric Use [8.4]), and 9 elderly subjects (14%, ≥65 years of age). The oldest subject was 75 years of age.

There were 17 subjects with a 3-week cycle and 46 subjects with a 4-week cycle. There were 51 subjects (81%) with common variable immunodeficiency as their primary diagnosis, followed by X-linked agammaglobulinemia and ‘Other’ (9.5% each). The intent to treat (ITT) population included 58 subjects and was used for efficacy analysis.

The primary endpoint of the study was to assess the efficacy of BIVIGAM in preventing serious bacterial infections (SBIs) defined as rate of <1.0 cases of bacterial pneumonia, bacteremia/septicemia, osteomyelitis/septic arthritis, visceral abscess, and bacterial meningitis per person-year. Secondary efficacy parameters included time to first SBI and time to first infection of any kind/seriousness, days on antibiotics (excluding prophylaxis), days off school/work due to infections, all confirmed infections of any kind or seriousness, and hospitalizations due to infection.

During the 12-month study period, two serious acute bacterial infections occurred in two subjects with an onset date between the first infusion of BIVIGAM and the first follow-up visit, inclusive. Thus, the mean event rate of serious, acute, bacterial infections per year was 0.037 (with an upper 1-sided 99% confidence interval of 0.101, which met the study’s primary efficacy endpoint).

The two SBIs were cases of bacterial pneumonia. Thirty-three percent of subjects had days off work or school due to an infection. Of the 197 infections reported, 2 resulted in hospitalization. Results for the pediatric subjects were similar to those for the adult subjects. (see Table 7).

Table 7: Summary of Efficacy Results in Subjects with PI

Number of Subjects (ITT Population) | 58
Total Number of person-yearsa | 53.5
Infections
Number of confirmed serious acute bacterial infectionsb | 2
Rate of SBIs (SBIs/total person-years) | 0.037
Total infections | 197
Infections per subject per year | 3.7
Antibiotic usec
Number of subjects (%) | 50 (86%)
Days per subject per year | 39.1
Days off school/work due to infections
Number of persons with days off of school or work due to infections (%) | 21 (36%)
Total days (%) | 122 (0.6%)
Days per subject per year | 2.3
Hospitalization
Number of subjects (%) | 2 (3.4%)
Number of Days | 11 (0.06%)
Days per subject per year | 0.21
SBI = serious bacterial infections.
a Person-years: Person-time in years with 2 decimals = (the Final Clinical Visit Date - the Day 0 date+1) / 365.25, where the final clinical visit date is defined as the specimen collection date of the final clinical visit for urinalysis, or the specimen collection date for the clinical laboratory tests at the final clinical visit and Day 0 date is the start date of the first BIVIGAM infusion.
b Defined as bacterial pneumonia, bacterial meningitis, bacteremia/septicemia, osteomyelitis/septic arthritis, and visceral abscess.
c The calculation of antibiotic use excludes 8 subjects who were on antibiotics throughout the study either prophylactically or for ongoing or recurrent conditions.

Pediatric Only Study

A prospective, open-label, single-arm, multi-center study evaluating the safety, efficacy, and PK of BIVIGAM was conducted in 16 pediatric subjects; 3 subjects ≥2 to <6, 5 subjects ≥6 to <12, and 8 subjects ≥12 to ≤16 years, with confirmed and documented clinical diagnosis of PID, including hypogammaglobulinemia or agammaglobulinemia. Of the 16 subjects enrolled, all (100%) were male, and the majority (80%) were white.

Subjects received a BIVIGAM infusion administrated every 3 or 4 weeks (based on the dose and schedule depending on their prior treatment regimen) for approximately 5 months. Average BIVIGAM doses administered (all infusions, both infusion regimens combined, values rounded) ranged from 368 to 1077 mg/kg in the 2 to <6 years age group, from 312 to 693 mg/kg in the 6 to <12 years age group and from 350 to 795 mg/kg in the 12 to 16 years age group.

The efficacy analysis is based on the incidence of acute serious bacterial infections (SBIs). SBIs encompass bacteremia/sepsis, bacterial meningitis, osteomyelitis/septic arthritis, bacterial pneumonia, or visceral abscess. No acute SBIs occurred during the mean observation period of 152 days, yielding a mean number of acute SBI episodes per person-year of 0.0. No other serious infections, or hospitalizations due to infections occurred, and no subjects required IV antibiotics during the study.

Trough Total IgG levels were maintained above 500 mg/dL in all subjects throughout the study. There were no apparent differences in the Total IgG or subclass concentrations before the first and last infusions.

15 REFERENCES

1. Gupta N, Ahmed I, Nissel-Horowitz S, Patel D, Mehrotra B. Intravenous gammaglobulin-associated acute renal failure. Am J Hematol 2001; 66:151-152.
2. Cayco, A.V., M.A. Perazella, and J.P. Hayslett. Renal insufficiency after intravenous immune globulin therapy: a report of two cases and an analysis of the literature. J Am Soc Nephrol 1997; 8:1788-1794.
3. Steinberger BA, Ford SM, Coleman TA. Intravenous immune globulin therapy results in post-infusional hyperproteinemia, increased serum viscosity, and pseudohyponatremia. Am J Hematol 2003; 73:97-100.
4. Dalakas MC. High-dose intravenous immunoglobulin and serum viscosity: risk of precipitating thromboembolic events. Neurology 1994; 44:223-226.
5. Woodruff RK, Grigg AP, Firkin FC, Smith IL. Fatal thrombotic events during treatment of autoimmune thrombocytopenia with intravenous immunoglobulin in elderly patients. Lancet 1986; 2:217-218.
6. Wolberg AS, Kon RH, Monroe DM, Hoffman M. Coagulation factor XI is a contaminant in intravenous immunoglobulin preparations. Am J Hematol 2000; 65:30-34.
7. Casteels-Van Daele, M., et al. Intravenous immune globulin and acute aseptic meningitis [letter]. N Engl J Med 1990; 323:614-615.
8. Kato, E., et al. Administration of immune globulin associated with aseptic meningitis [letter]. Jama 1988; 259:3269-3271.
9. Scribner, C.L., et al. Aseptic meningitis and intravenous immunoglobulin therapy [editorial, comment]. Ann Intern Med 1994; 121:305-306.
10. Copelan EA, Stohm PL, Kennedy MS, Tutschka PJ. Hemolysis following intravenous immune globulin therapy. Transfusion 1986; 26:410-412.
11. Thomas MJ, Misbah SA, Chapel HM, Jones M, Elrington G, Newsom-Davis J. Hemolysis after high-dose intravenous Ig. Blood 1993; 15:3789.
12. Wilson JR, Bhoopalam N, Fisher M. Hemolytic anemia associated with intravenous immunoglobulin. Muscle & Nerve 1997; 20:1142-1145.
13. Kessary-Shoham H, Levy Y, Shoenfeld Y, Lorber M, Gershon H. In vivo administration of intravenous immunoglobulin (IVIg) can lead to enhanced erythrocyte sequestration. J Autoimmune 1999; 13:129-135.
14. Rizk A, Gorson KC, Kenney L, Weinstein R. Transfusion-related acute lung injury after the infusion of IVIG. Transfusion 2001; 41:264-268.
15. Siber GA, Werner BG, Halsey NA, et al. Interference of immune globulin with measles and rubella immunization. J Pediatr 1993; 122:204-211.
16. Salisbury D, Ramsay M, Noakes K, eds. Immunisation against infectious disease. The Stationery Office (TSO), London: UK Department of Health; 2009:426.
17. Skvaril F. Qualitative and quantitative aspects of IgG subclasses in i.v. immunoglobulin preparations. In: Nydegger UE, ed. Immunotherapy. London: Academic Press; 1981:118-122.
18. French M. Serum IgG subclasses in normal adults. Monogr Allergy 1986, 19:100-107.

16 HOW SUPPLIED/STORAGE AND HANDLING

BIVIGAM is supplied in a single-use, tamper-evident vial. The components used in the packaging for BIVIGAM are not made with natural rubber latex.

BIVIGAM is supplied in the following sizes:

NDC Number | Size | Grams Protein
69800-6502-1 | 50mL | 5
69800-6503-1 | 100mL | 10

Storage
Store at 2 to 8°C (36 to 46°F) for up to 36 months from date of manufacture. Do not freeze.

Product may be stored up to 4 weeks at ≤ 25°C (77°C). After storage at room temperature product must be used or discarded.

Special Precautions for Storage
Do not freeze or heat. Do not use any solutions that have been frozen or heated.
Allow refrigerated product to come to room temperature before use.

Do not use after expiration date.

Shelf-life
BIVIGAM may be stored until expiration date on vial packaging at 2 to 8°C (36 to 46°F).

Product may be stored up to 4 weeks at ≤ 25°C (77°C). After storage at room temperature product must be used or discarded.

Incompatibilities
Do not dilute.
BIVIGAM should be infused using a separate line by itself, without mixing with other intravenous fluids or medications the patient may be receiving.

17 PATIENT COUNSELING INFORMATION

17.1 Acute Renal Dysfunction and Acute Renal Failure

Instruct patients to immediately report symptoms of decreased urine output, sudden weight gain, fluid retention/edema, and/or shortness of breath. Such symptoms may suggest kidney damage (see Boxed Warning, Warnings and Precautions [5.3]).

17.2 Thrombosis

Instruct patients to immediately report symptoms of thrombosis. These symptoms may include: pain and/or swelling of an arm or legs/feet with warmth over the affected area, discoloration of an arm or leg, unexplained shortness of breath, acute chest pain or discomfort that worsens on deep breathing, unexplained rapid pulse, numbness or weakness on one side of the body. (see Warnings and Precautions [5.1]).

17.3 Aseptic Meningitis Syndrome (AMS)

Instruct patients to immediately report signs and symptoms of AMS. These symptoms include severe headache, neck stiffness, drowsiness, fever, sensitivity to light, painful eye movements, nausea and vomiting (see Warnings and Precautions [5.5]).

17.4 Hemolysis

Instruct patients to immediately report signs and symptoms of hemolysis. These symptoms include fatigue, increased heart rate, yellowing of skin or eyes, dark-colored urine (see Warnings and Precautions [5.6]).

17.5 Transfusion-Related Acute Lung Injury (TRALI)

Instruct patients to immediately report signs and symptoms of TRALI. These symptoms include trouble breathing, chest pain, blue lips or extremities, fever (see Warnings and Precautions [5.7]).

17.6 Transmissible Infectious Agents

Inform patients that BIVIGAM is made from human plasma and may contain infectious agents that can cause disease. While the risk that BIVIGAM can transmit an infection has been reduced by screening plasma donors for prior exposure, testing donated plasma, and inactivating or removing certain viruses during manufacturing, patients should report any symptoms that concern them (see Description [11] and Warnings and Precautions [5.8]).

17.7 Live Virus Vaccines

Inform patients that BIVIGAM can interfere with their immune response to live viral vaccines (e.g., measles, mumps, rubella, and varicella), and instruct patients to notify their healthcare professional of this potential interaction when they are receiving vaccinations (see Drug Interactions [7]).